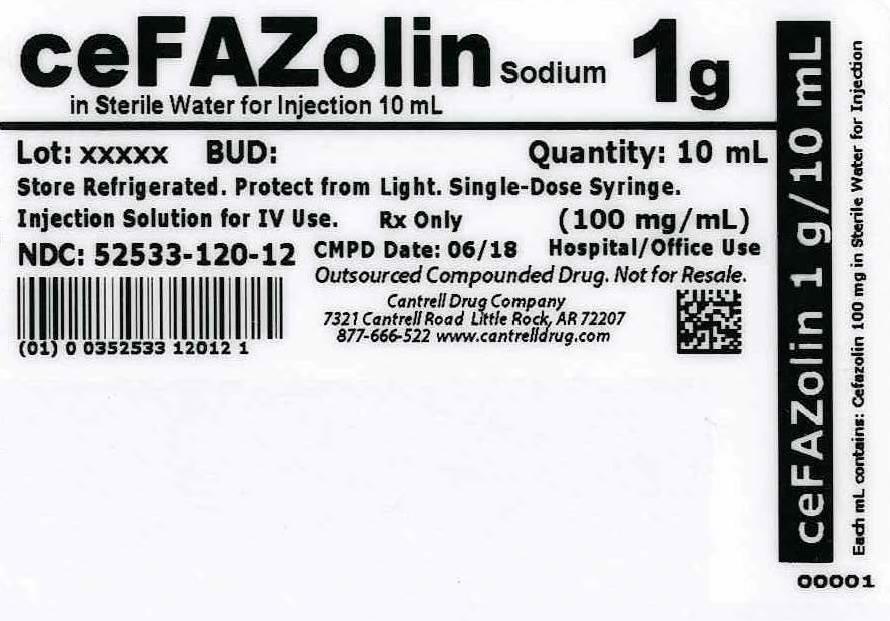 DRUG LABEL: Cefazolin Sodium
NDC: 52533-120 | Form: INJECTION, SOLUTION
Manufacturer: Cantrell Drug Company
Category: prescription | Type: HUMAN PRESCRIPTION DRUG LABEL
Date: 20140527

ACTIVE INGREDIENTS: Cefazolin Sodium 100 mg/1 mL
INACTIVE INGREDIENTS: Water

Cefazolin Sodium 1 g in Sterile Water for Injection 10 mL Syringe